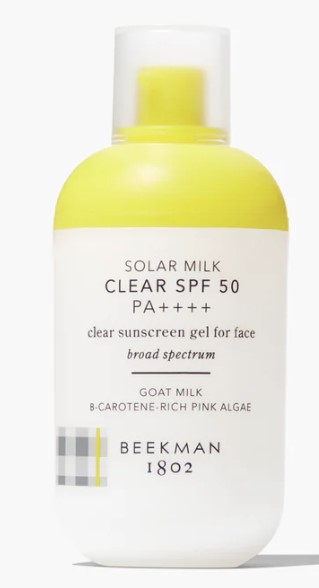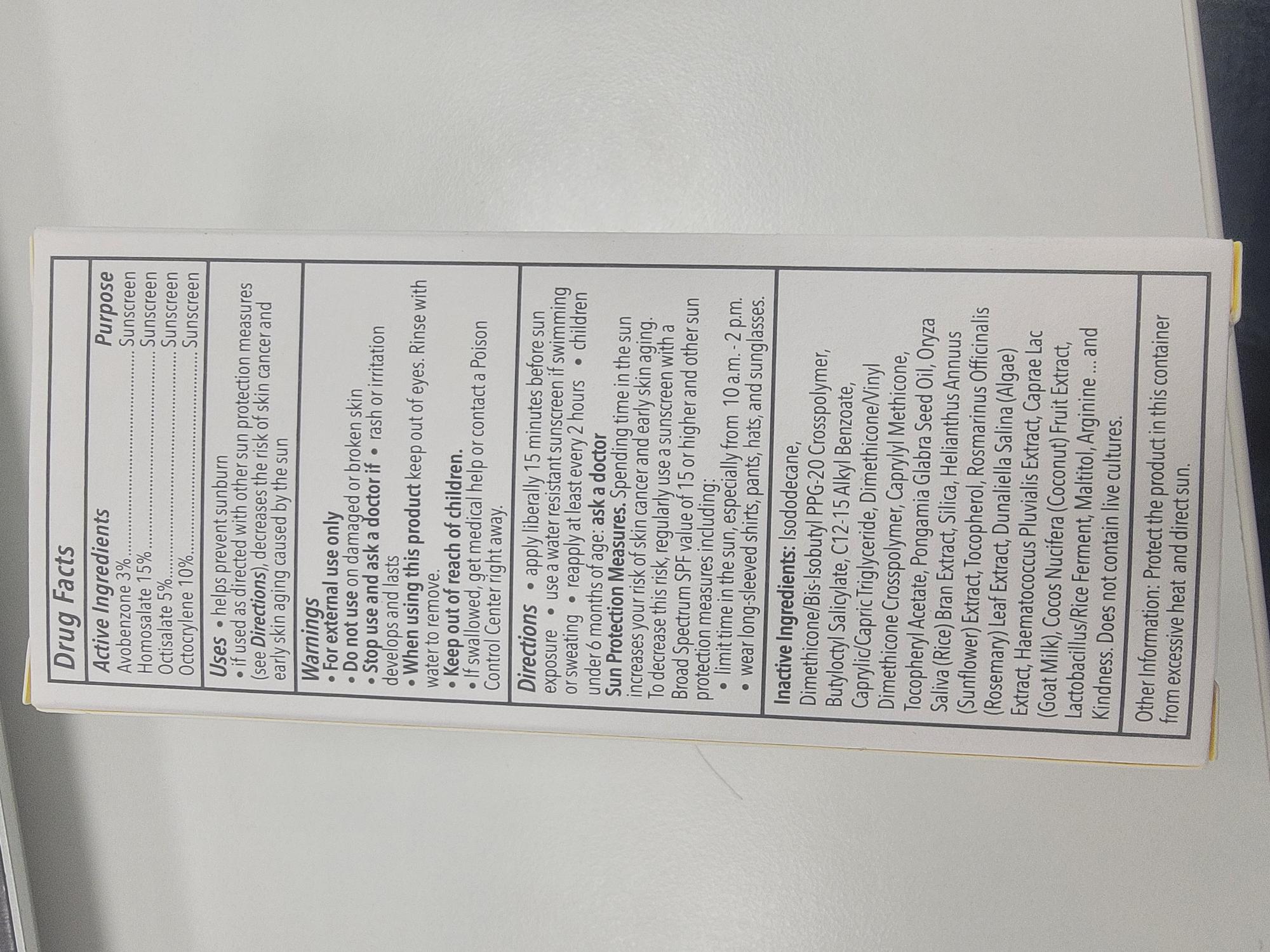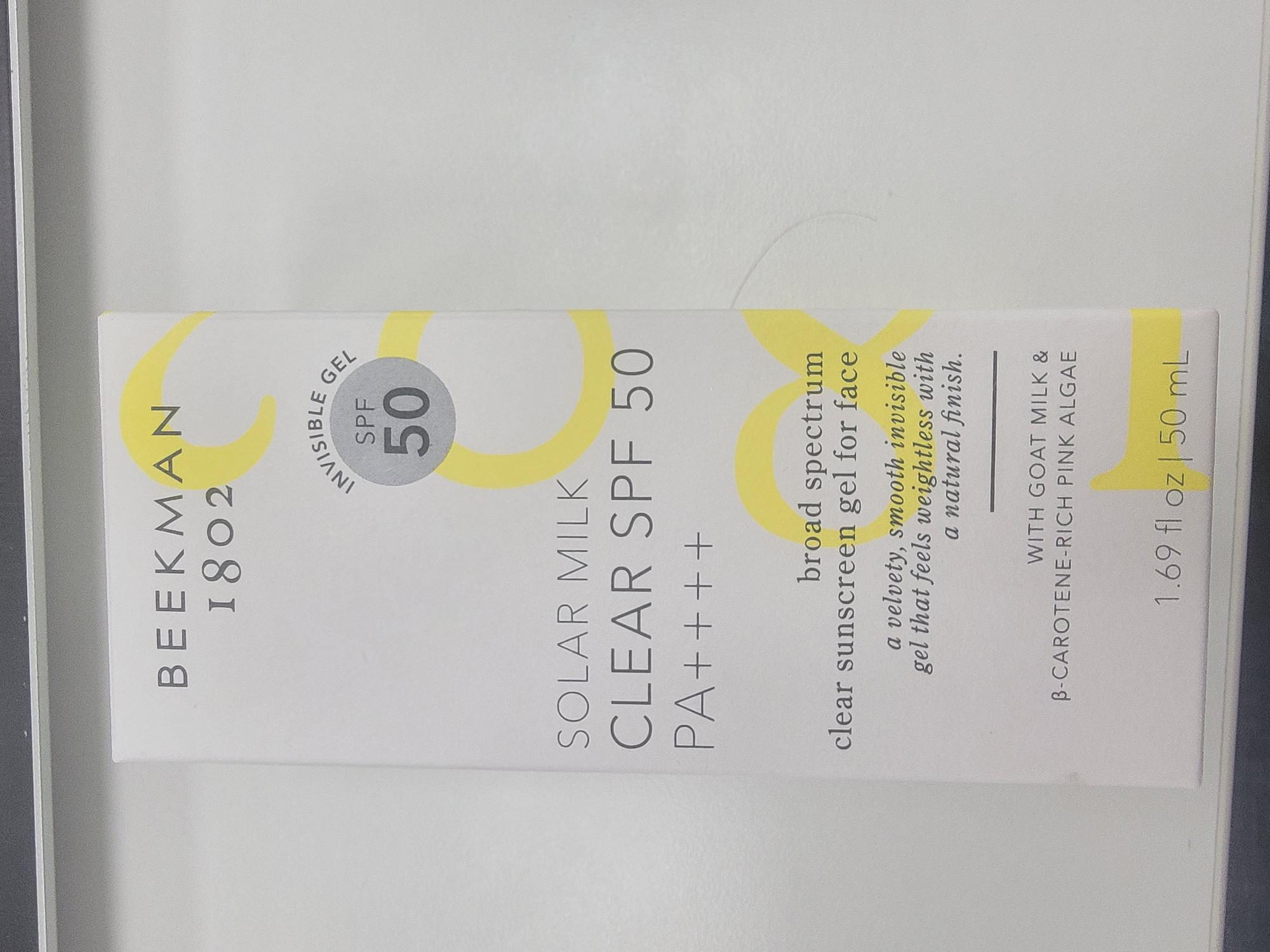 DRUG LABEL: SOLAR MILK SPF50
NDC: 68577-197 | Form: GEL
Manufacturer: COSMAX USA, CORPORATION
Category: otc | Type: HUMAN OTC DRUG LABEL
Date: 20241224

ACTIVE INGREDIENTS: AVOBENZONE 3 mg/1 mL; HOMOSALATE 15 mg/1 mL; OCTOCRYLENE 10 mg/1 mL; OCTISALATE 5 mg/1 mL
INACTIVE INGREDIENTS: MALTITOL; ARGININE; ORYZA SATIVA (RICE) BRAN; TOCOPHEROL; ROSEMARY; COCOS NUCIFERA (COCONUT) FRUIT; ISODODECANE; BUTYLOCTYL SALICYLATE; DIMETHICONE/VINYL DIMETHICONE CROSSPOLYMER (SOFT PARTICLE); HAEMATOCOCCUS PLUVIALIS; C12-15 ALKYL BENZOATE; CAPRYLIC/CAPRIC TRIGLYCERIDE; CAPRYLYL METHICONE; SILICA; GOAT MILK; HELIANTHUS ANNUUS FLOWERING TOP; DIMETHICONE/BIS-ISOBUTYL PPG-20 CROSSPOLYMER

BEEKMAN SOLAR MILK CLEAR SPF50

Active Ingredients

Avobenzone 3%

Homosalate 15%

Octisalate 5%

Octocrylene 10%

Purpose

Sunscreen

USES

- helps prevent sunburn
- if used as directed with other sun protection measures (see Directions), decreases the risk of skin cancer and early skin aging caused by the sun

Warnings

- For external use only

Do not use on damaged or broken skin

Stop use and ask a doctor if

- rash or irritation develops and lasts

When using this product keep out of eyes. Rinse with water to remove.

Keep out of reach of children. If swallowed, get medical help or contact a Poison Control Center right away.

DIRECTIONS

- apply liberally 15 minutes before sun exposure
- use a water resistant sunscreen if swimming or sweating
- reapply at least every 2 hours
- children under 6 months of age ask a doctor Sun Protection Measures. Spending time in the sun increases you risk of skin cancer and ealy skin aging. To decrease this risk, regularly use a sunscreen with a Broad Spectrum SPF value of 15 or higher and other sun protection measures including:
- limit time in the sun, especially from 10 a.m. - 2 p.m.
- wear long-sleeved shirts, pants, hats, and sunglasses.

Inactive Ingredients

Isododecane, Dimethicone/Bis-lsobutyl PPG-20 Crosspolymer, Butyloctyl Salicylate, C12-15 Alkyl Benzoate, Caprylic/Capric Triglyceride, Dimethicone/Vinyl Dimethicone Crosspolymer, Caprylyl Methicone, Tocopheryl Acetate Pongamia Glabra Seed Oil, Oryza Saliva (Rice) Bran Extract, Silica, Helianthus Annuus (Sunflower) Extract, Tocopherol, Rosmarinus Officinalis (Rosemary) Leaf Extract, Dunaliella Salina (Algae) Extract, Haematococcus Pluvialis Extract, Caprae Lac (Goat Milk), Cocos Nucifera (Coconut) Fruit Extract, Lactobacillus/Rice Ferment, Maltitol, Arginine